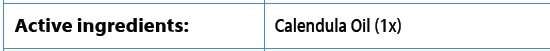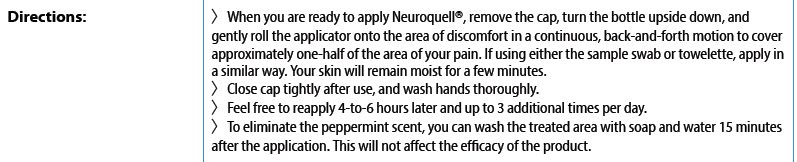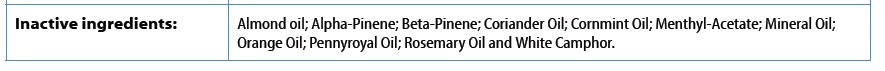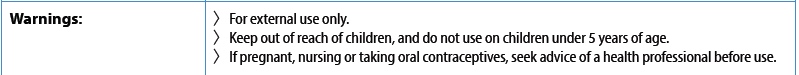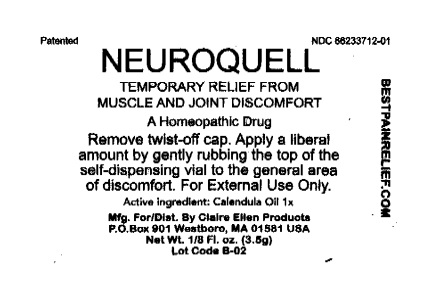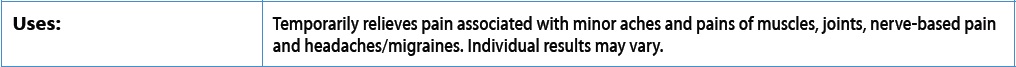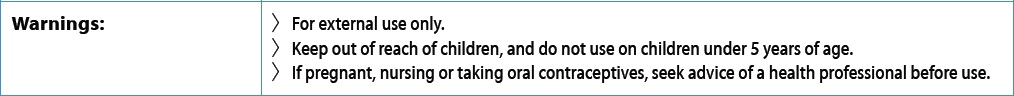 DRUG LABEL: Neuroquell
NDC: 66233-712 | Form: OIL
Manufacturer: Atlantic Management Resources Inc
Category: homeopathic | Type: HUMAN OTC DRUG LABEL
Date: 20220711

ACTIVE INGREDIENTS: CALENDULA OFFICINALIS FLOWERING TOP 0.005 g/1 g
INACTIVE INGREDIENTS: ORANGE OIL 0.007 g/1 g; CORIANDER OIL 0.002 g/1 g; MINERAL OIL 0.001 g/1 g; ALMOND OIL 0.005 g/1 g; ROSEMARY OIL 0.06 g/1 g; CAMPHOR OIL, WHITE 0.05 g/1 g; PENNYROYAL OIL 0.04 g/1 g; MENTHA ARVENSIS LEAF OIL 0.83 g/1 g

Neuroquell